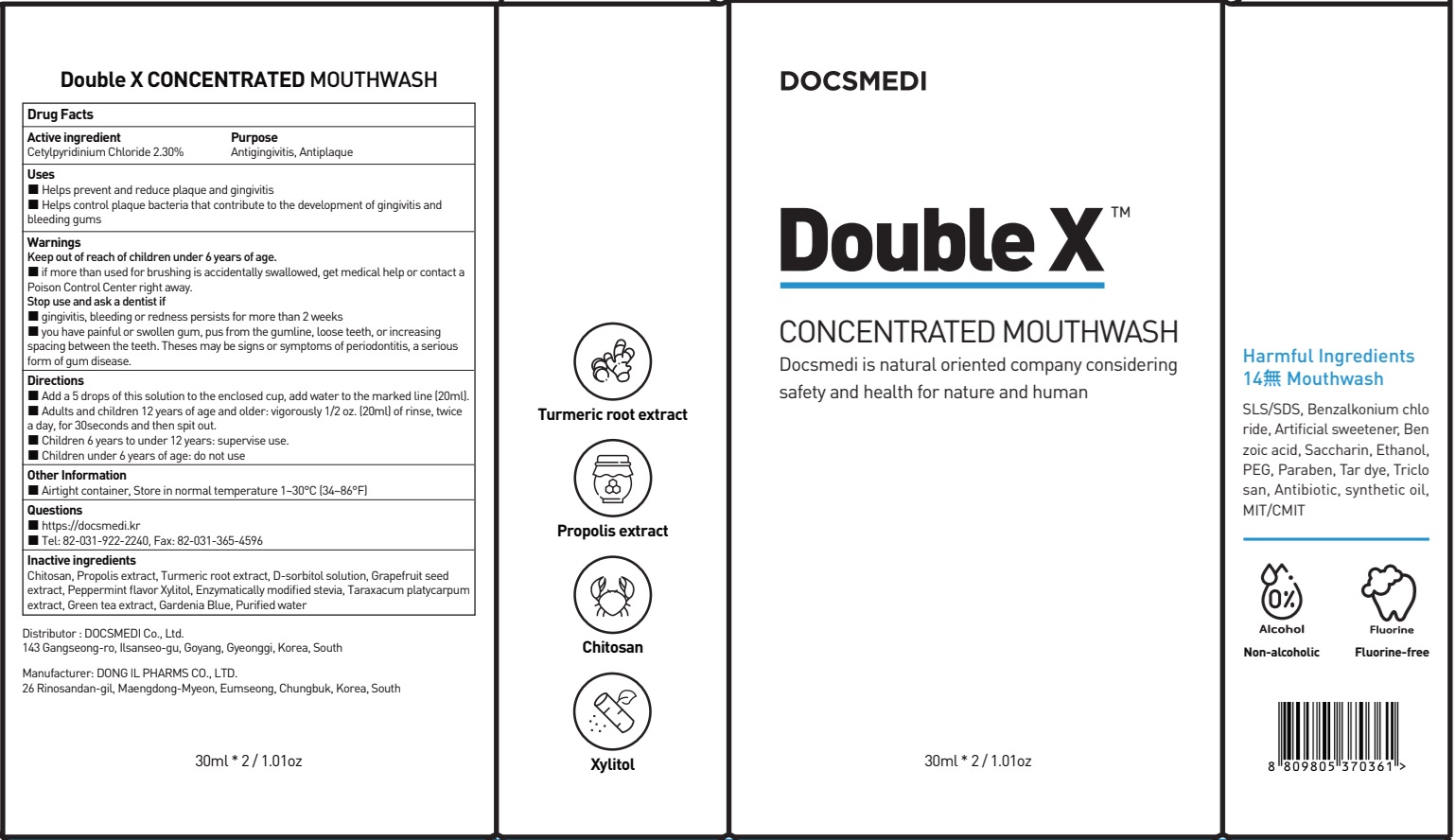 DRUG LABEL: Double X CONCENTRATED
NDC: 76670-0012 | Form: MOUTHWASH
Manufacturer: DOCSMEDI Co., Ltd.
Category: otc | Type: HUMAN OTC DRUG LABEL
Date: 20250122

ACTIVE INGREDIENTS: CETYLPYRIDINIUM CHLORIDE 2.3 g/100 mL
INACTIVE INGREDIENTS: PROPOLIS WAX; TURMERIC; SORBITOL

ACTIVE INGREDIENT

Cetylpyridinium Chloride 2.30%

INACTIVE INGREDIENTS

Chitosan, Propolis extract, Turmeric root extract, D-sorbitol solution, Grapefruit seed extract, Peppermint flavor Xylitol, Enzymatically modified stevia, Taraxacum platycarpum extract, Green tea extract, Gardenia Blue, Purified water

PURPOSE

Antigingivitis, Antiplaque

WARNINGS

Keep out of reach of children under 6 years of age.
■ if more than used for brushing is accidentally swallowed, get medical help or contact a Poison Control Center right away.
Stop use and ask a dentist if
■ gingivitis, bleeding or redness persists for more than 2 weeks
■ you have painful or swollen gum, pus from the gumline, loose teeth, or increasing spacing between the teeth. Theses may be signs or symptoms of periodontitis, a serious form of gum disease.

Keep out of reach of children under 6 years of age.
■ if more than used for brushing is accidentally swallowed, get medical help or contact a Poison Control Center right away.

Uses

■ Helps prevent and reduce plaque and gingivitis
■ Helps control plaque bacteria that contribute to the development of gingivitis and bleeding gums

Directions

■ Add a 5 drops of this solution to the enclosed cup, add water to the marked line (20ml).
■ Adults and children 12 years of age and older: vigorously 1/2 oz. (20ml) of rinse, twice a day, for 30seconds and then spit out.
■ Children 6 years to under 12 years: supervise use.
■ Children under 6 years of age: do not use

Other Information

■ Airtight container, Store in normal temperature 1~30°C (34~86°F)

Questions

■ https://docsmedi.kr

■ Tel: 82-031-922-2240, Fax: 82-031-365-4596